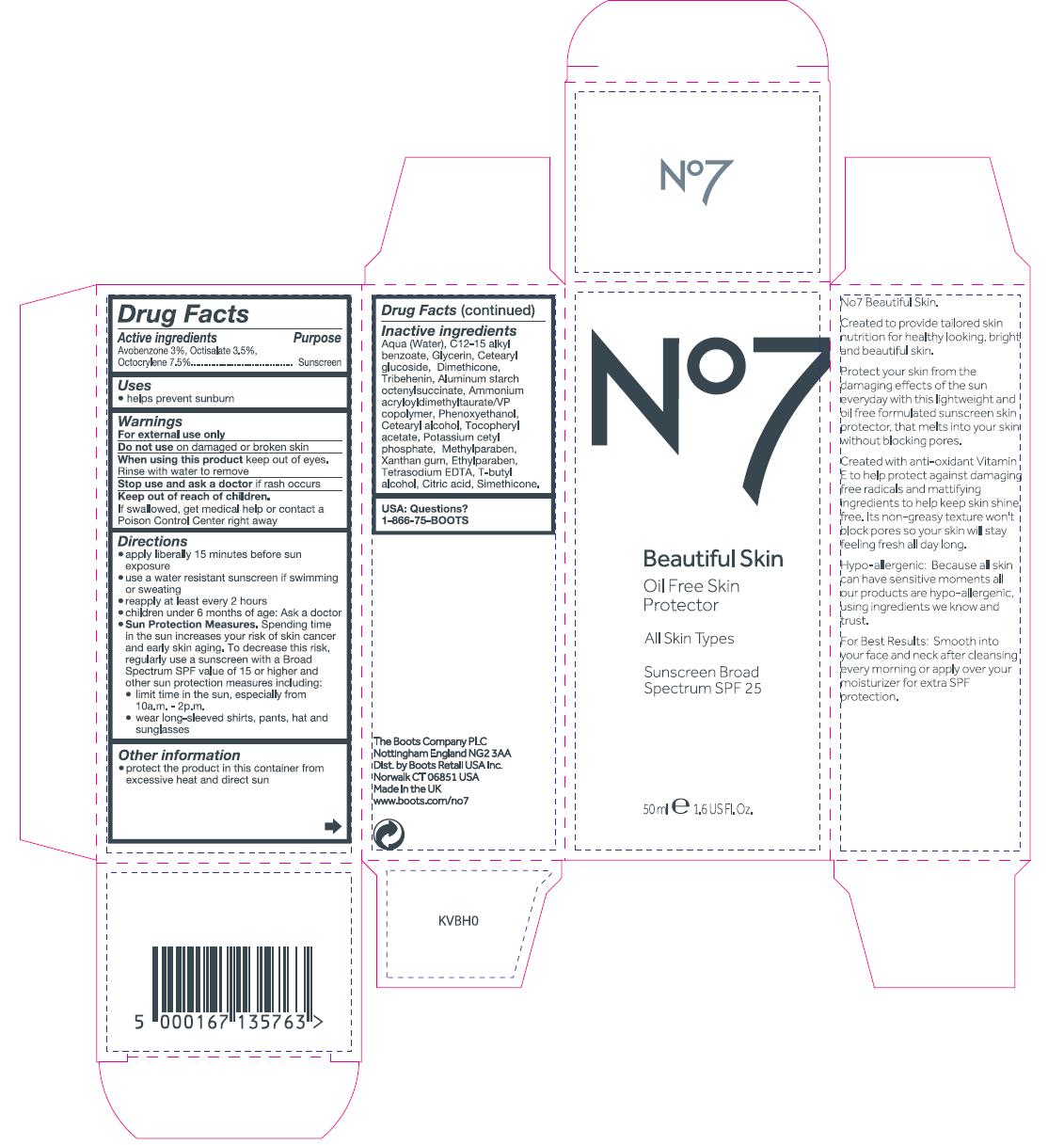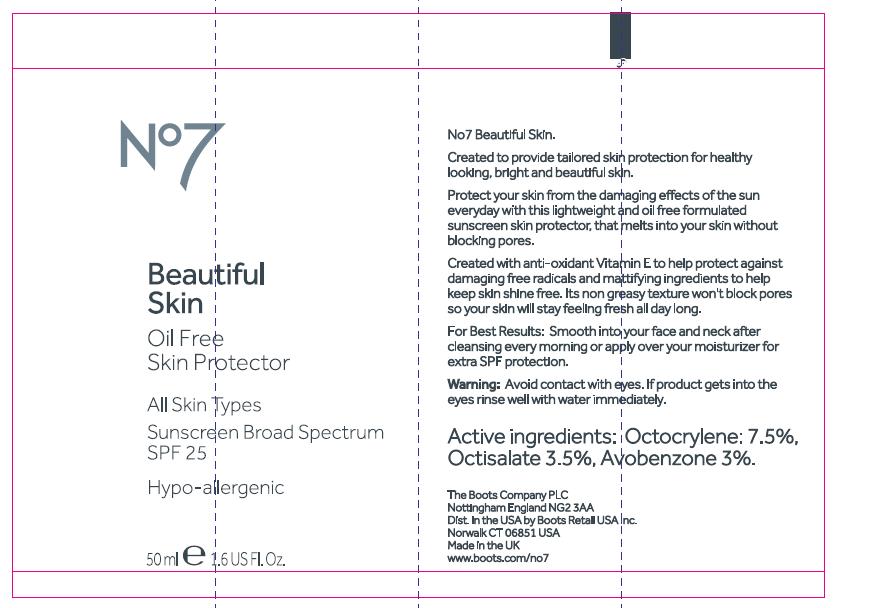 DRUG LABEL: No7 Beautiful Skin Oil Free Skin Protector All Skin Types SPF 25
NDC: 68472-108 | Form: CREAM
Manufacturer: Boots Retail USA Inc
Category: otc | Type: HUMAN OTC DRUG LABEL
Date: 20120502

ACTIVE INGREDIENTS: Avobenzone 1.5 mL/50 mL; Octisalate 1.75 mL/50 mL; Octocrylene 3.25 mL/50 mL
INACTIVE INGREDIENTS: Water; ALKYL (C12-15) BENZOATE; GLYCERIN; CETEARYL GLUCOSIDE; Dimethicone; TRIBEHENIN; ALUMINUM STARCH OCTENYLSUCCINATE; AMMONIUM ACRYLOYLDIMETHYLTAURATE/VP COPOLYMER; PHENOXYETHANOL; CETOSTEARYL ALCOHOL; .ALPHA.-TOCOPHEROL ACETATE; POTASSIUM CETYL PHOSPHATE; METHYLPARABEN; XANTHAN GUM; ETHYLPARABEN; EDETATE SODIUM; TERT-BUTYL ALCOHOL; CITRIC ACID MONOHYDRATE

Carton and tube labelling

Inactive Ingredients

Aqua (water), C12-15 alkyl benzoate, Glycerin, Cetearyl glucoside, Dimethicone, Tribehenin, Aluminum starch octenylsuccinate, Ammonium acryloyldimethyltaurate/VP copolymer, Phenoxyethanol, Cetearyl alcohol, Tocopheryl acetate, Potassium cetyl phosphate, Methylparaben, Xanthan gum, Ethylparaben, Tetrasodium EDTA, T-butyl alcohol, Citric acid, Simethicone

USA: Questions? 1-866-75-BOOTS

The Boots Company PLC Nottingham England NG2 3AA

Dist. by Boots Retail USA Inc. Norwalk CT 06851 USA

Made in the UK

DESCRIPTION

No7 Beautiful Skin.
Created to provide tailored skin nutrition for healthy looking, bright and beautiful skin.
Protect your skin from the damaging effects of the sun everyday with this lightweight and oil free formulated sunscreen skin protector that melts into your skin without blocking pores.
Created with anti-oxidant Vitamin E to help protect against damaging free radicals and mattifying ingredients to help keep skin shine free. It's non-greasy texture won't block pores so your skin will stay feeling fresh all day long.
Hypo-allergenic: Because all skin can have sensitive moments all our products are hypo-allergenic, using ingredients we know and trust.

INDICATIONS AND USAGE

For Best Results: Smooth into your face and neck after cleansing every morning or apply over your moisturizer for extra SPF protection.

Active Ingredients

Avobenzone 3%, Octisalate 3.5%, Octocrylene 7.5%

Purpose

Sunscreen

Uses

Helps prevent sunburn

Warnings

For external use only

Do not use on damaged or broken skin

When using this product keep out of eyes. Rinse with water to remove.

Stop use and ask a doctor if rash occurs

Keep out of reach of children.

If swallowed, get medical help or contact a Poison Control Center right away

Directions

Apply liberally 15 minutes before sun exposure

Use a water resistant sunscreen if swimming or sweating

Reapply at least every 2 hours

Children under 6 months of age: ask a doctor

Sun Protection Measures. Spending time in the sun increases your risk of skin cancer and early skin aging. To decrease this risk, regularly use a sunscreen with a broad spectrum SPF value of 15 or higher and other sun protection measures including:

limit time in the sun, especially from 10a.m. - 2p.m.

wear long-sleeved shirts, pants, hat and sunglasses

Other Information

Protect the product in this container from excessive heat and direct sun

DESCRIPTION

TUBE TEXT

No7 Beautiful Skin.

Created to provide tailored skin protection for healthy looking, bright and beautiful skin.

Protect your skin from the damaging effects of the sun everyday with this lightweight and oil free formulated sunscreen skin protector, that melts into your skin without blocking pores.

Created with anti-oxidant Vitamin E to help protect against damaging free radicals and mattifying ingredients to help keep skin shine free. It's non-greasy texture won't block pores so your skin will stay feeling fresh all day long.

For Best Results: Smooth into your face and neck after cleansing every morning or apply over your moisturizer for extra SPF protection.

WARNINGS

TUBE TEXT

Warning: Avoid contact with eyes. If product gets into the eyes rinse well with water immediately.

ACTIVE INGREDIENT

TUBE TEXT

Active ingredients: Octocrylene 7.5%, Octisalate 3.5%, Avobenzone 3%.

PATIENT COUNSELING INFORMATION

TUBE TEXT

The Boots Company PLC

Nottingham England NG2 3AA

Dist. in the USA by Boots Retail USA Inc.

Norwalk CT 06851 USA

Made in the UK

www.boots.com/no7

PACKAGE LABEL

No7 Beautiful Skin

Oil Free Skin Protector

All Skin Types

Sunscreen Broad Spectrum SPF 25

50ml 1.6 US Fl.Oz.

PACKAGE LABEL

No7 Beautiful Skin

Oil Free Skin Protector

All Skin Types

Sunscreen Broad Spectrum SPF 25

Hypo-allergenic

50ml 1.6 US Fl.Oz.